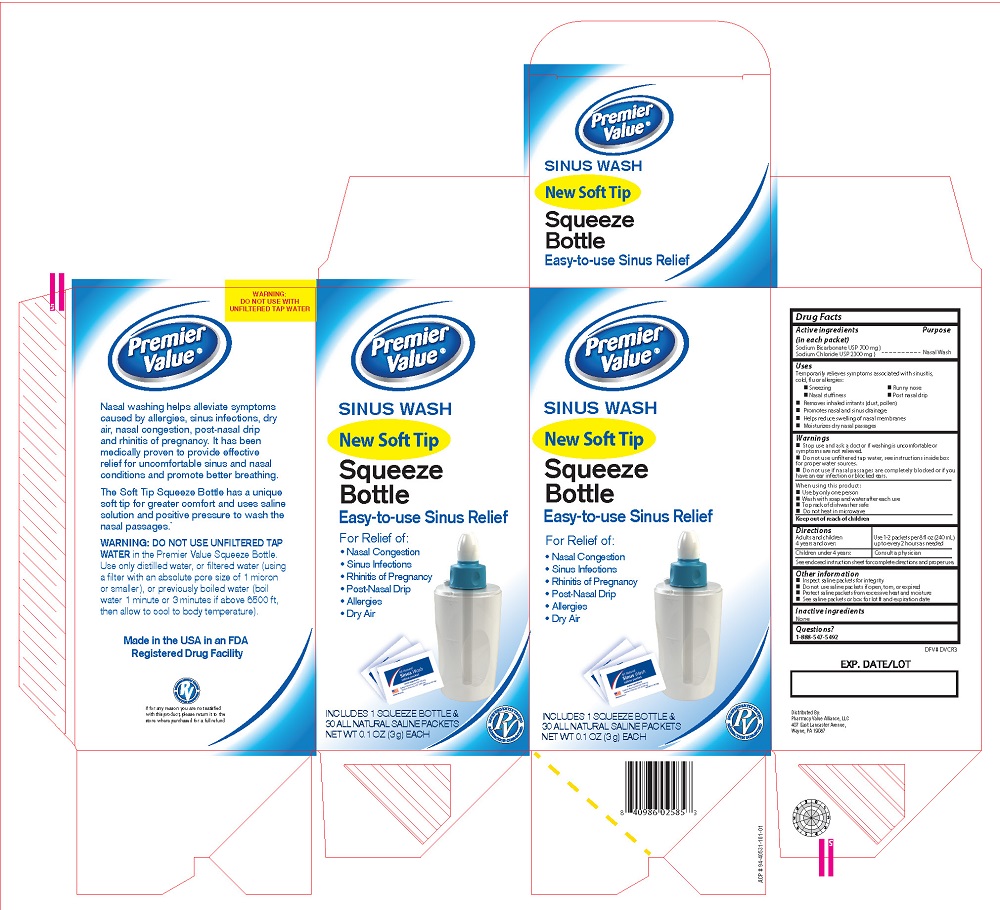 DRUG LABEL: Soft Tip Squeeze bottle Sinus Wash
NDC: 68016-452 | Form: KIT | Route: NASAL
Manufacturer: Premier Value
Category: otc | Type: HUMAN OTC DRUG LABEL
Date: 20251210

ACTIVE INGREDIENTS: SODIUM CHLORIDE 2300 mg/3000 mg; SODIUM BICARBONATE 700 mg/3000 mg
INACTIVE INGREDIENTS: WATER

Premier Value Sinus Wash Squeeze bottle- New Soft Tip

Purpose

Nasal Wash

Active ingredients

(in each packet)

Sodium Bicarbonate USP (700 mg)

Sodium Chloride USP (2300 mg)

Uses

Temporarily relieves symptoms associated with

sinusitis, cold, flu or allergies

-Sneezing

-Nasal Stuffiness

-Runny nose

-Post nasal drip

Removes inhaled irritants (dust, pollen)

Removes nasal and sinus drainage

Helps reduce swelling of nasal membranes

Moisturizes dry nasal passages

Keep out of reach of children

Warnings

Stop use and ask a doctor if washing is uncomfortable

or symptoms are not relieved.

Do not use unfiltered tap water. see instructions inside box for proper water sources

Do not use if nasal passages are completely blocked or if you have an ear infection or blocked ears.

Directions

Adults and children 4 years and over: Use 1-2 packets per 8 fl oz (240 mL) up to every 2 hours as needed.

Children under 4 years: Consult a physician

See enclosed instruction sheet for complete directions and proper use.

Other Information

-Inspect saline packets for integrity

-Do not use saline packets if open or torn

-Protect saline packets from excessive heat and moisture

-See saline packets or box for lot number and expiration date

Questions?

1-888-547-5492

Inactive Ingredients

None